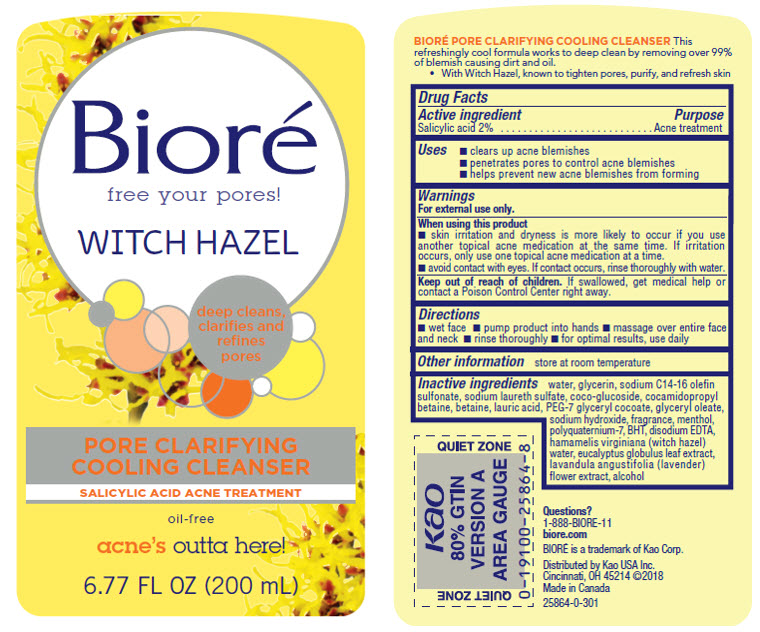 DRUG LABEL: Biore
NDC: 10596-188 | Form: LIQUID
Manufacturer: Kao USA Inc.
Category: otc | Type: HUMAN OTC DRUG LABEL
Date: 20250101

ACTIVE INGREDIENTS: SALICYLIC ACID 2 g/100 mL
INACTIVE INGREDIENTS: GLYCERYL OLEATE; WITCH HAZEL; EUCALYPTUS GLOBULUS LEAF; LAVANDULA ANGUSTIFOLIA FLOWER; BUTYLATED HYDROXYTOLUENE; EDETATE DISODIUM; SODIUM LAURETH SULFATE; COCO GLUCOSIDE; COCAMIDOPROPYL BETAINE; WATER; GLYCERIN; SODIUM HYDROXIDE; MENTHOL; BETAINE; SODIUM C14-16 OLEFIN SULFONATE; LAURIC ACID; PEG-7 GLYCERYL COCOATE; POLYQUATERNIUM-7 (70/30 ACRYLAMIDE/DADMAC; 1600 KD); ALCOHOL

Biore Witch Hazel Pore Clarifying Cooling Cleanser

BIORE PORE CLARIFYING COOLING CLEANSER

This refreshingly cool formula works to deep clean by removing over 99% of blemish causing dirt and oil.

- With Witch Hazel, known to tighten pores, purify, and refresh skin

Drug Facts

Active ingredient

Salicylic acid 2%

Purpose

Acne treatment

Uses

- clears up acne blemishes
- penetrates pores to control acne blemishes
- helps prevent new acne blemishes from forming

Warnings

For external use only.

When using this product

- skin irritation and dryness is more likely to occur if you use another topical acne medication at the same time. If irritation occurs, only use one topical acne medication at a time.
- avoid contact with eyes. If contact occurs, rinse thoroughly with water.

Keep out of reach of children. If swallowed, get medical help or contact a Poison Control Center right away.

Directions

- wet face
- pump product into hands
- massage over entire face and neck
- rinse thoroughly
- for optimal results, use daily

Other information

store at room temperature

Inactive ingredients

water, glycerin, sodium C14-16 olefin sulfonate, sodium laureth sulfate, coco-glucoside, cocamidopropyl betaine, betaine, lauric acid, PEG-7 glyceryl cocoate, glyceryl oleate, sodium hydroxide, fragrance, menthol, polyquaternium-7, BHT, disodium EDTA, hamamelis virginiana (witch hazel) water, eucalyptus globulus leaf extract, lavandula angustifolia (lavender) flower extract, alcohol

Questions?

1-888-BIORE-11

www.biore.com

BIORE is a trademark of Kao Corp.

Distributed by Kao USA Inc.

Cincinnati, OH 45214 ©2018

Made in Canada

PACKAGE LABEL

Biore

free your pores!

WITCH HAZEL

deep cleans, clarifies and refines pores

PORE CLARIFYING COOLING CLEANSER

SALICYLIC ACID ACNE TREATMENT

oil-free

acne's outta here!

6.77 FL OZ (200 mL)